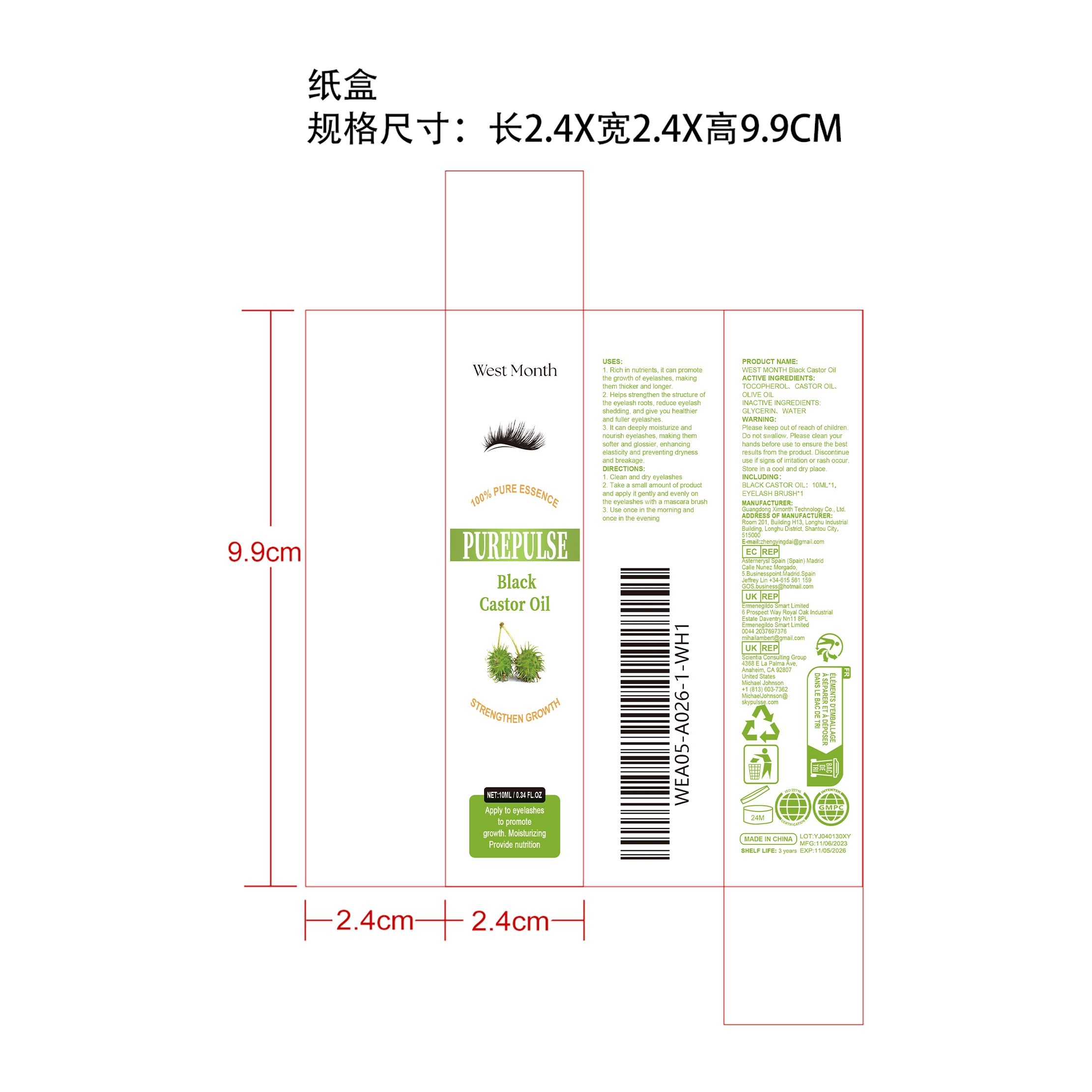 DRUG LABEL: WEST MONTH Black Castor Oil
NDC: 84660-063 | Form: OIL
Manufacturer: Guangdong Ximonth Technology Co., Ltd.
Category: otc | Type: HUMAN OTC DRUG LABEL
Date: 20241102

ACTIVE INGREDIENTS: OLIVE OIL 1 mg/10 mg; TOCOPHEROL 2 mg/10 mg; CASTOR OIL 1 mg/10 mg
INACTIVE INGREDIENTS: GLYCERIN 4 mg/10 mg; WATER 2 mg/10 mg

Active Ingredient(s)

TOCOPHEROL、CASTOR OIL、OLIVE OIL

PURPOSE

1. Rich in nutrients, it can promote the growth of eyelashes, making them thicker and longer.
2. Helps strengthen the structure of the eyelash roots, reduce eyelash shedding, and give you healthier and fuller eyelashes.
3. It can deeply moisturize and nourish eyelashes, making them softer and glossier, enhancing elasticity and preventing dryness and breakage.

Use

1. Clean and dry eyelashes
2. Take a small amount of product and apply it gently and evenly on the eyelashes with a mascara brush
3. Use once in the morning and once in the evening

Warning

Please keep out of reach of children.Do not swallow.Please clean your hands before use to ensure the best results from the product.Discontinue use if signs of irritation or rash occur.Store in a cool and dry place.

Do not use

Discontinue use if signs of irritation or rash occur.

STOP USE

Discontinue use if signs of irritation or rash occur.

KEEP OUT OF REACH OF CHILDREN

Please keep out of reach of children. Do not swallow.

STORAGE AND HANDLING

Store in a cool and dry place.

INACTIVE INGREDIENT

GLYCERIN、WATER